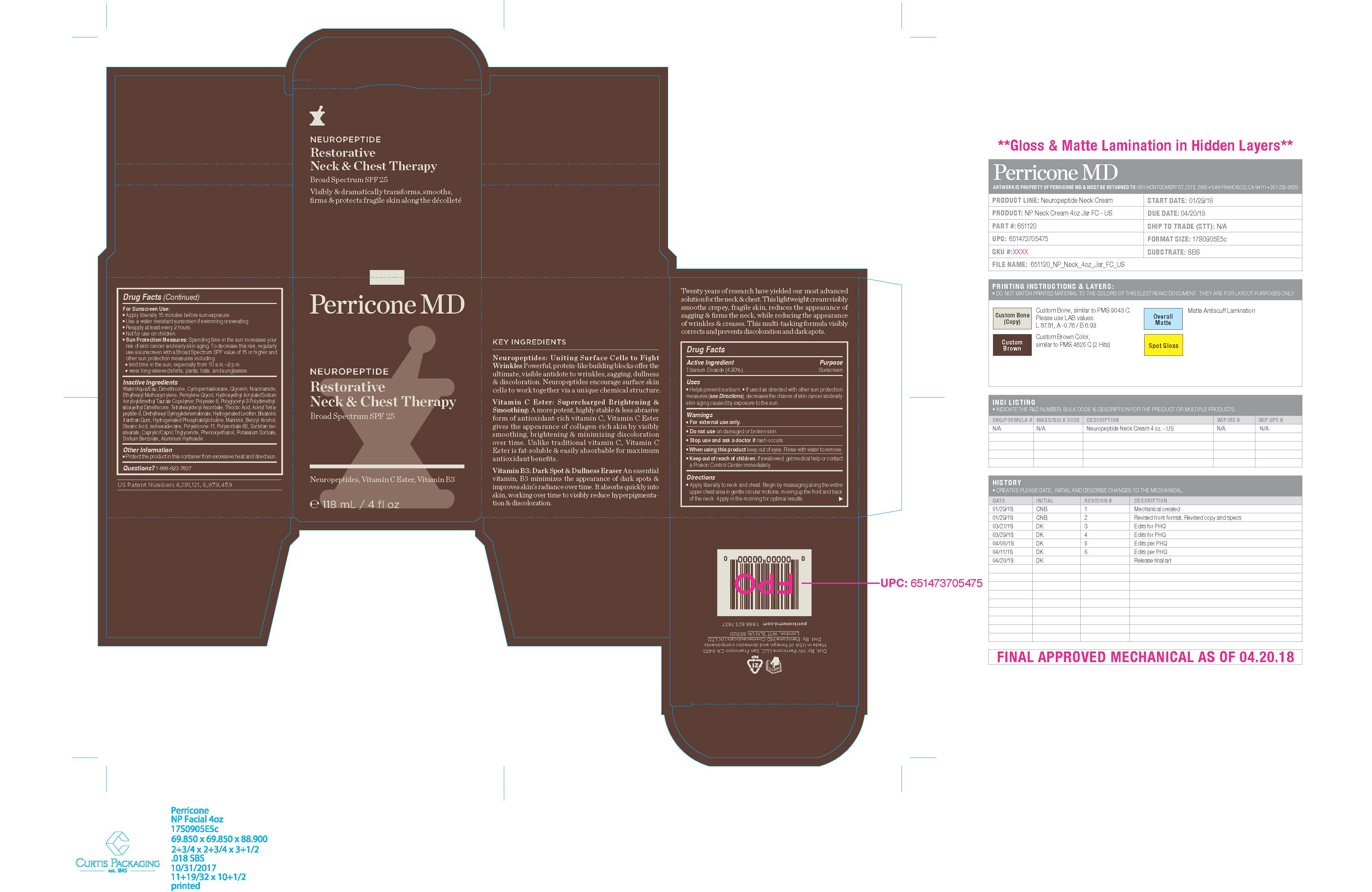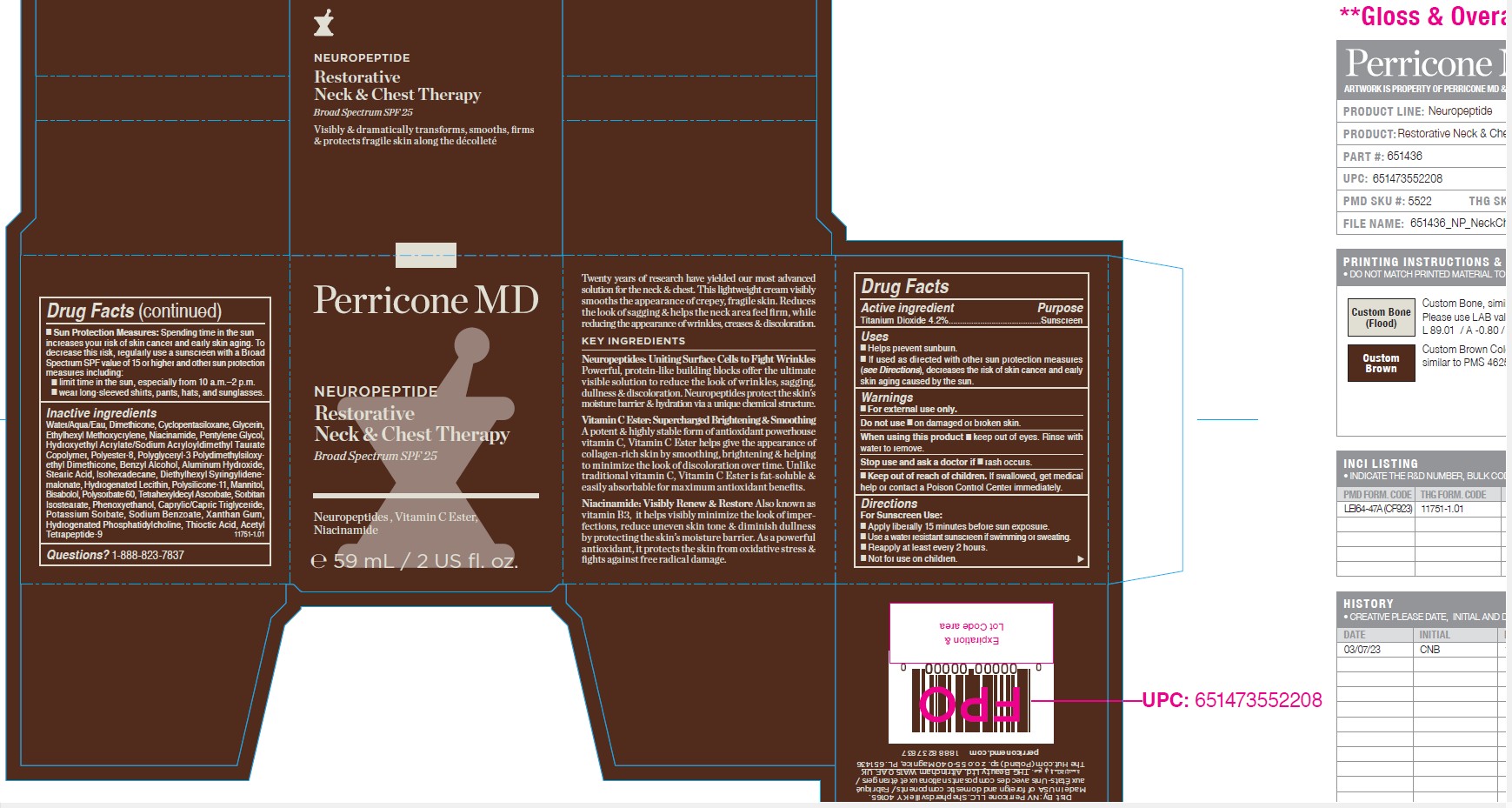 DRUG LABEL: Perricone MD Neuropeptide Restorative Neck and Chest Therapy Broad Spectrum SPF 25
NDC: 84448-447 | Form: CREAM
Manufacturer: THG Beauty USA LLC
Category: otc | Type: HUMAN OTC DRUG LABEL
Date: 20251028

ACTIVE INGREDIENTS: TITANIUM DIOXIDE 4.2 g/100 mL
INACTIVE INGREDIENTS: XANTHAN GUM; HYDROGENATED SOYBEAN PHOSPHATIDYLCHOLINE; THIOCTIC ACID; POLYGLYCERYL-3 POLYDIMETHYLSILOXYETHYL DIMETHICONE (4000 MPA.S); HYDROGENATED SOYBEAN LECITHIN; MANNITOL; DIMETHICONE; HYDROXYETHYL ACRYLATE/SODIUM ACRYLOYLDIMETHYL TAURATE COPOLYMER (45000 MPA.S AT 1%); POLYSORBATE 60; WATER; CYCLOMETHICONE 5; ETHYLHEXYL METHOXYCRYLENE; TETRAHEXYLDECYL ASCORBATE; SORBITAN ISOSTEARATE; DIETHYLHEXYL SYRINGYLIDENEMALONATE; ISOHEXADECANE; STEARIC ACID; GLYCERIN; NIACINAMIDE; PENTYLENE GLYCOL; BENZYL ALCOHOL; ALUMINUM HYDROXIDE; LEVOMENOL; PHENOXYETHANOL; MEDIUM-CHAIN TRIGLYCERIDES; ACETYL TETRAPEPTIDE-9; POLYESTER-8 (1400 MW, CYANODIPHENYLPROPENOYL CAPPED); POTASSIUM SORBATE; SODIUM BENZOATE

ACTIVE INGREDIENT

Titanium Dioxide 4.2%

PURPOSE

Sunscreen

INDICATIONS AND USAGE

■ Helps prevent sunburn. ■ If used as directed with other sun protection measures (see Directions), decreases the risk of skin cancer and early skin aging caused by the sun.

WARNINGS

For external use only.

Do not use ■ on damaged or broken skin.

When using this product ■ keep out of eyes. Rinse with water to remove

Stop use and ask a doctor if ■ rash occurs.

Keep out of reach of children. If swallowed, get medical help or contact a Poison Control Center immediately.

DOSAGE AND ADMINISTRATION

For Sunscreen Use: ■ Apply liberally 15 minutes before sun exposure. ■ Use a water resistant sunscreen if swimming or sweating. ■ Reapply at least every 2 hours. ■ Not for use on children.

■ Sun Protection Measures: Spending time in the sun increases your risk of skin cancer and early skin aging. To decrease this risk, regularly use a sunscreen with a Broad Spectrum SPF value of 15 or higher and other sun protection measures including: ■ limit time in the sun, especially from 10 a.m.–2 p.m. ■ wear long-sleeved shirts, pants, hats, and sunglasses.

INACTIVE INGREDIENT

Water/Aqua/Eau, Dimethicone, Cyclopentasiloxane, Glycerin, Ethylhexyl Methoxycrylene, Niacinamide, Pentylene Glycol, Hydroxyethyl Acrylate/Sodium Acryloyldimethyl Taurate Copolymer, Polyester-8, Polyglyceryl-3 Polydimethylsiloxyethyl Dimethicone, Benzyl Alcohol, Aluminum Hydroxide, Stearic Acid, Isohexadecane, Diethylhexyl Syringylidenemalonate, Hydrogenated Lecithin, Polysilicone-11, Mannitol, Bisabolol, Polysorbate 60, Tetrahexyldecyl Ascorbate, Sorbitan Isostearate, Phenoxyethanol, Caprylic/Capric Triglyceride, Potassium Sorbate, Sodium Benzoate, Xanthan Gum, Hydrogenated Phosphatidylcholine, Thioctic Acid, Acetyl Tetrapeptide-9

QUESTIONS

1-888-823-7837